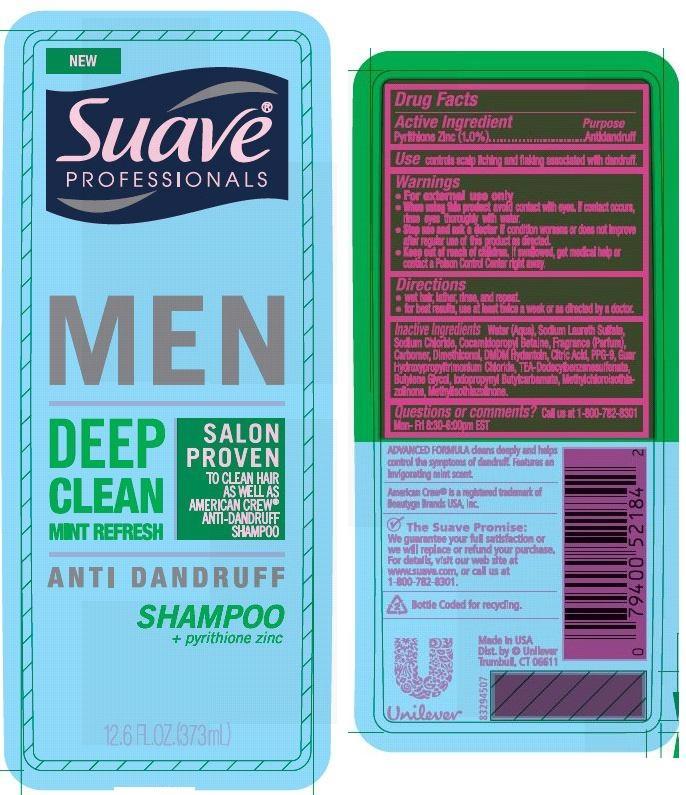 DRUG LABEL: Suave
NDC: 64942-1436 | Form: SHAMPOO
Manufacturer: Conopco Inc. d/b/a Unilever
Category: otc | Type: HUMAN OTC DRUG LABEL
Date: 20150924

ACTIVE INGREDIENTS: Pyrithione Zinc 1.0 g/100 mL
INACTIVE INGREDIENTS: WATER; SODIUM LAURETH SULFATE; COCAMIDOPROPYL BETAINE; SODIUM CHLORIDE; CARBOMER HOMOPOLYMER TYPE C; BUTYLENE GLYCOL; DMDM HYDANTOIN; TRIETHANOLAMINE DODECYLBENZENESULFONATE; IODOPROPYNYL BUTYLCARBAMATE; CITRIC ACID MONOHYDRATE; PPG-9; METHYLCHLOROISOTHIAZOLINONE; METHYLISOTHIAZOLINONE; GUAR HYDROXYPROPYLTRIMONIUM CHLORIDE (1.7 SUBSTITUENTS PER SACCHARIDE); DIMETHICONOL (100000 CST)

Suave Men Deep Clean Mint Refresh Anti Dandruff Shampoo

Active Ingredient

Pyrithione Zinc (1.0%)

Purpose

Antidandruff

INDICATIONS AND USAGE

Use controls scalp itching and flaking associated with dandruff.

Warnings
For external use only

When using this product avoid contact with eyes. If contact occurs, rinse eyes thoroughly with water.

Stop use and ask a doctor if condition worsens or does not improve after regular use of this product as directed.

KEEP OUT OF REACH OF CHILDREN

Keep this and all drugs out of reach of children. If swallowed, get medical help or contact a Poison Control Center right away.

Directions

• wet hair, lather, rinse, and repeat.

• for best results, use at least twice a week or as directed by a doctor.

Inactive Ingredients

Water (Aqua), Sodium Laureth Sulfate, Sodium Chloride, Cocamidopropyl Betaine, Fragrance (Parfum), Carbomer, Dimethiconol, DMDM Hydantoin, Citric Acid, PPG-9, Guar Hydroxypropyltrimonium Chloride, TEA-Dodecylbenzenesulfonate, Butylene Glycol, Iodopropynyl Butylcarbamate, Methylchloroisothiazolinone, Methylisothiazolinone.

QUESTIONS

Question or comments? Call us at 1-800-782-8301 Mon-Fri 8:30-6:00pm EST